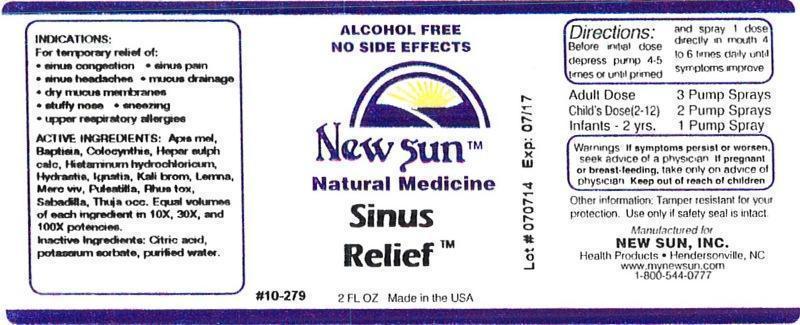 DRUG LABEL: Sinus Relief
NDC: 66579-0026 | Form: LIQUID
Manufacturer: New Sun Inc.
Category: homeopathic | Type: HUMAN OTC DRUG LABEL
Date: 20140717

ACTIVE INGREDIENTS: APIS MELLIFERA 10 [hp_X]/59 mL; BAPTISIA TINCTORIA ROOT 10 [hp_X]/59 mL; CITRULLUS COLOCYNTHIS FRUIT PULP 10 [hp_X]/59 mL; CALCIUM SULFIDE 10 [hp_X]/59 mL; HISTAMINE DIHYDROCHLORIDE 10 [hp_X]/59 mL; GOLDENSEAL 10 [hp_X]/59 mL; STRYCHNOS IGNATII SEED 10 [hp_X]/59 mL; POTASSIUM DICHROMATE 10 [hp_X]/59 mL; LEMNA MINOR 10 [hp_X]/59 mL; MERCURY 10 [hp_X]/59 mL; PULSATILLA VULGARIS 10 [hp_X]/59 mL; TOXICODENDRON PUBESCENS LEAF 10 [hp_X]/59 mL; SCHOENOCAULON OFFICINALE SEED 10 [hp_X]/59 mL; THUJA OCCIDENTALIS LEAFY TWIG 10 [hp_X]/59 mL
INACTIVE INGREDIENTS: CITRIC ACID MONOHYDRATE; POTASSIUM SORBATE; WATER

Sinus Relief

DOSAGE AND ADMINISTRATION

Directions: Before initial dose depress pump 4-5 times or until primed and spray 1 dose directly in mouth 4 to 6 times daily until symptoms improve.

Adult Dose: 3 Pump Sprays

Child's Dose (2-12): 2 Pump Sprays

Infants - 2 yrs: 1 Pump Spray

WARNINGS

Warnings: If symptoms persist or worsen, seek advice of physician. If pregnant or breast-feeding, take only on advice of physician.

Keep out of reach of children.

Other information: Tamper resistant for your protection. Use only if safety seal is intact.

PURPOSE

Indications: For temporary relief of: sinus congestion • sinus pain • sinus headaches • mucus drainage • dry mucus membranes • stuffy nose • sneezing • upper respiratory allergies

ACTIVE INGREDIENT

Active Ingredients: Apis mellifica, Baptisia tinctoria, Colocynthis, Hepar sulphuris calcareum, Histaminum hydrochloricum, Hydrastis canadensis, Ignatia amara, Kali bichromicum, Lemna minor, Mercurius vivus, Pulsatilla, Rhus toxicodendron, Sabadilla, Thuja occidentalis. Equal volumes of each ingredient in 10X, 30X, and 100X potencies.

Inactive Ingredient: Citric acid, potassium sorbate, purified water.

Indications: For temporary relief of:

- sinus congestion
- sinus pain
- sinus headaches
- mucus drainage
- dry mucus membranes
- stuffy nose
- sneezing
- upper respiratory allergies